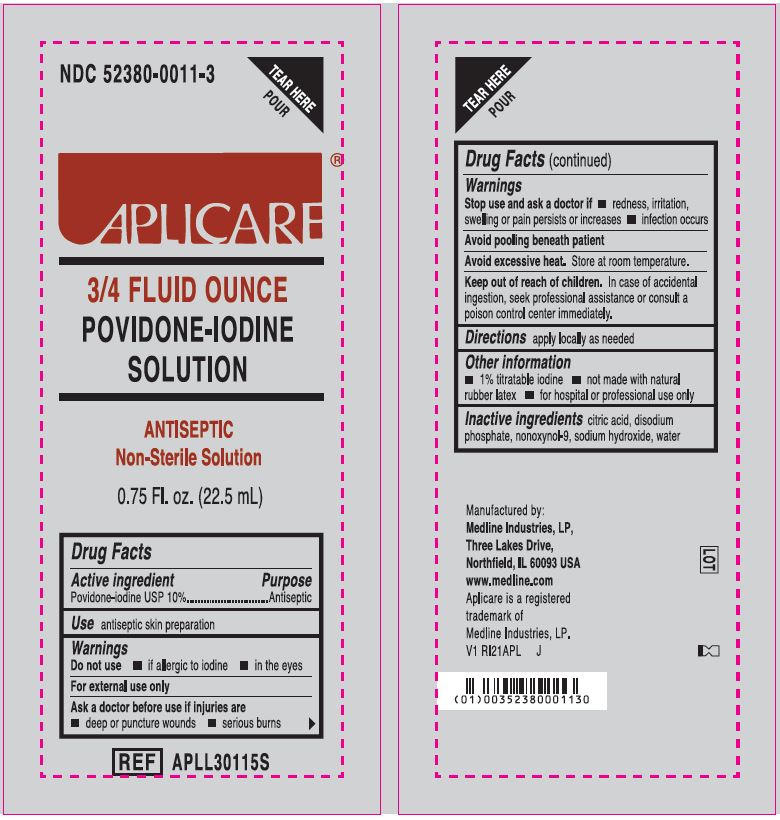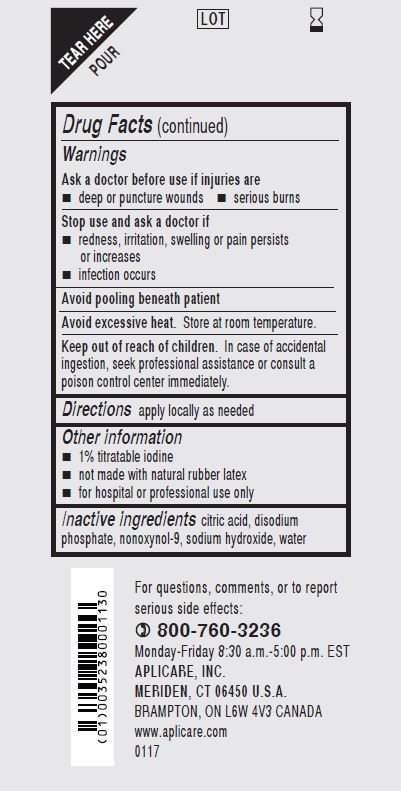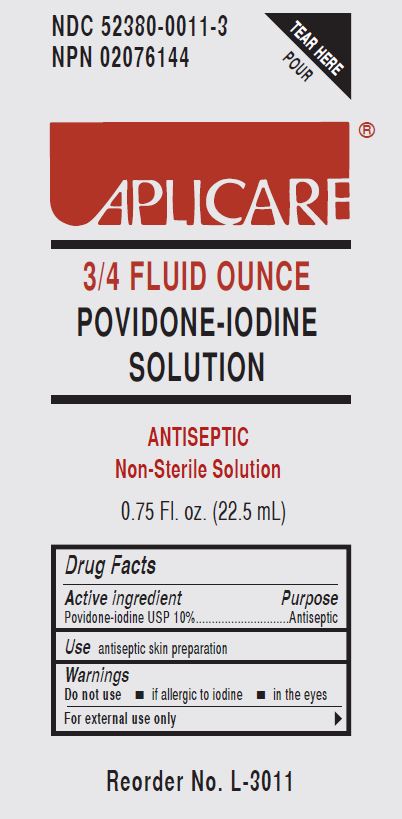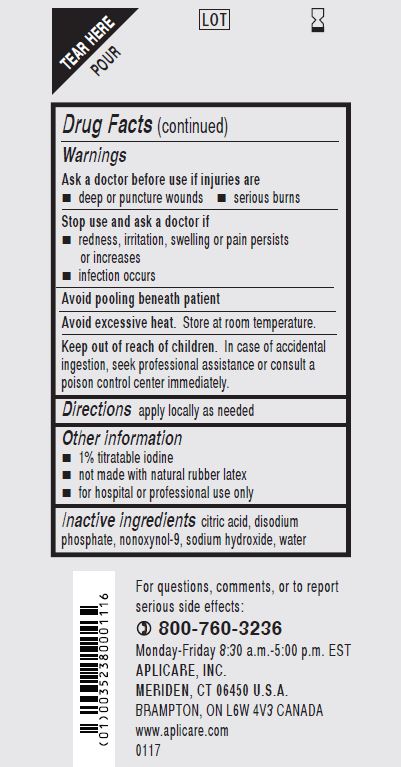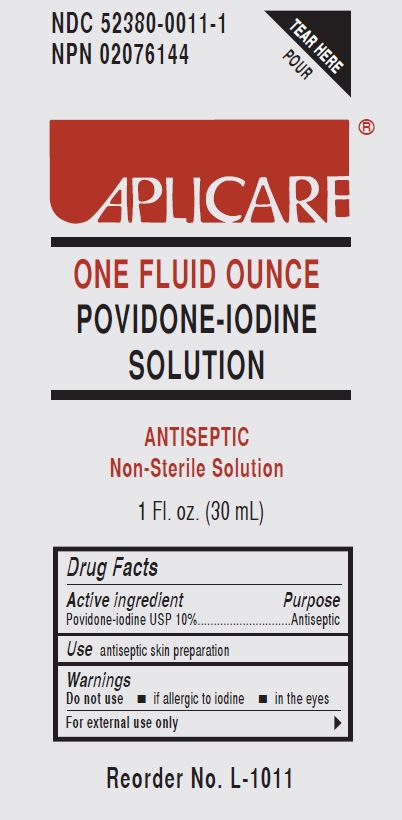 DRUG LABEL: Aplicare Povidone-Iodine
NDC: 52380-0011 | Form: SOLUTION
Manufacturer: Aplicare Products, LLC
Category: otc | Type: HUMAN OTC DRUG LABEL
Date: 20251107

ACTIVE INGREDIENTS: POVIDONE-IODINE 10 mg/1 mL
INACTIVE INGREDIENTS: CITRIC ACID MONOHYDRATE; SODIUM PHOSPHATE, DIBASIC; NONOXYNOL-9; SODIUM HYDROXIDE; WATER

0011 Povidone-Iodine (nonsterile)

Active ingredient

Povidone-iodine USP 10%

Purpose

Antiseptic

Use

antiseptic skin preparation

Warnings

- For external use only
- Avoid pooling beneath patient
- Avoid excessive heat. Store at room temperature

Do not use

- • if allergic to iodine
- • in the eyes

Ask a doctor before use if injuries are

- • deep or puncture wounds
- • serious burns

Stop use and ask a doctor if

- • redness, irritation, swelling or pain persists or increases
- • infection occurs

Keep out of reach of children.

In case of accidental ingestion, seek professional assistance or consult a poison control center immediately.

Directions

apply locally as needed

Other information

- • 1% titratable iodine
- • not made with natural rubber latex
- • for hospital or professional use only

Inactive ingredients

citric acid, disodium phosphate, nonoxynol-9, sodium hydroxide, water

Manufacturing Information

Manufactured by: Medline Industries, LP,

Three Lakes Drive, Northfield, IL 60093 USA

www.medline.com

1-800-MEDLINE

Aplicare is a registered trademark of Medline Industries, LP.

REF: APLL30115S